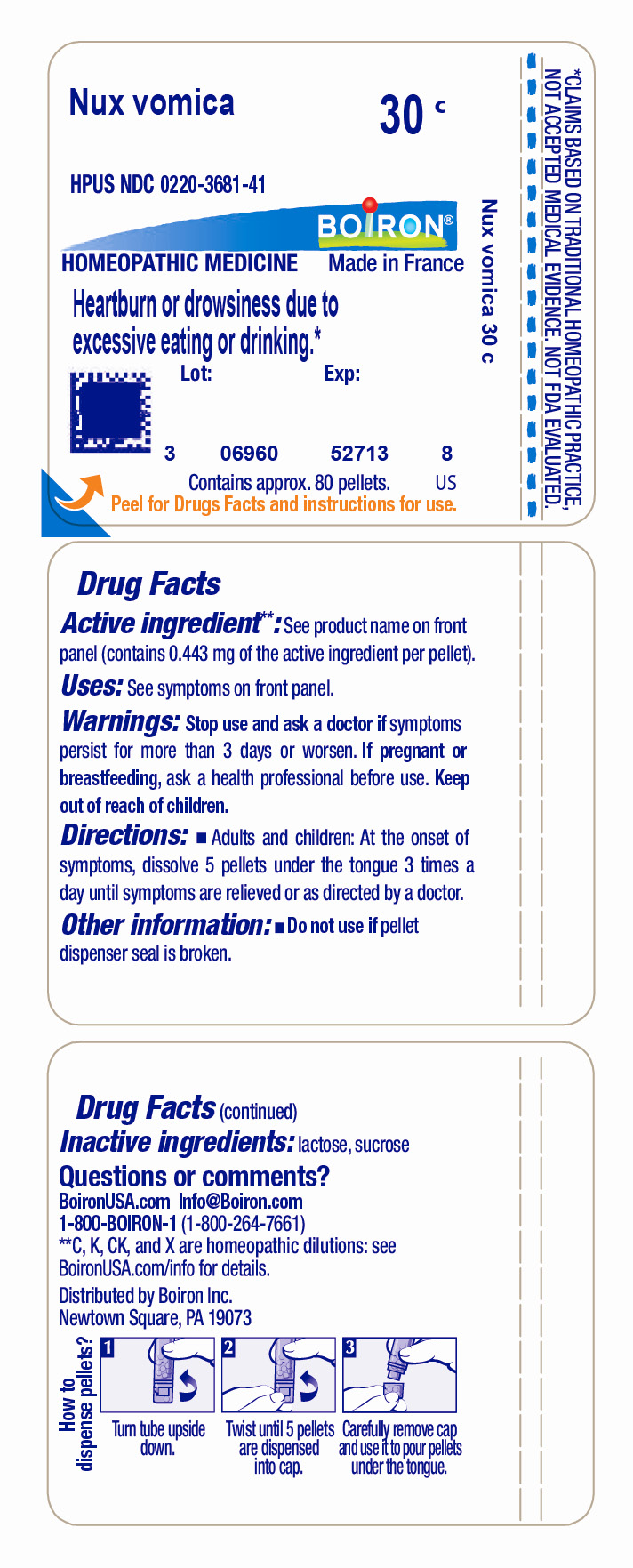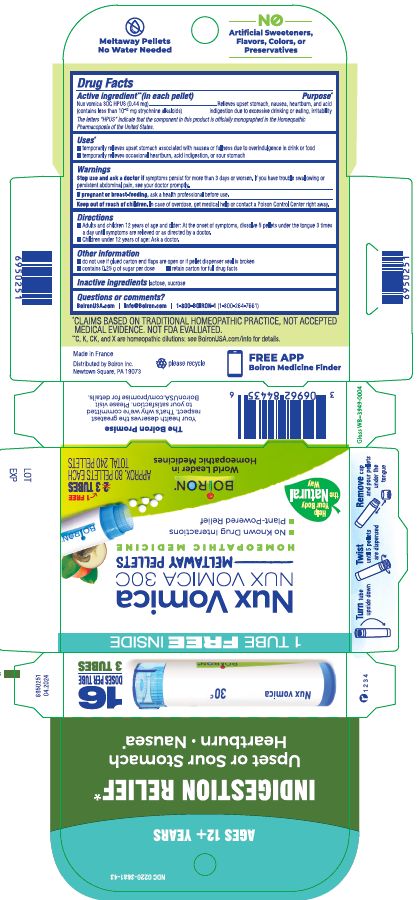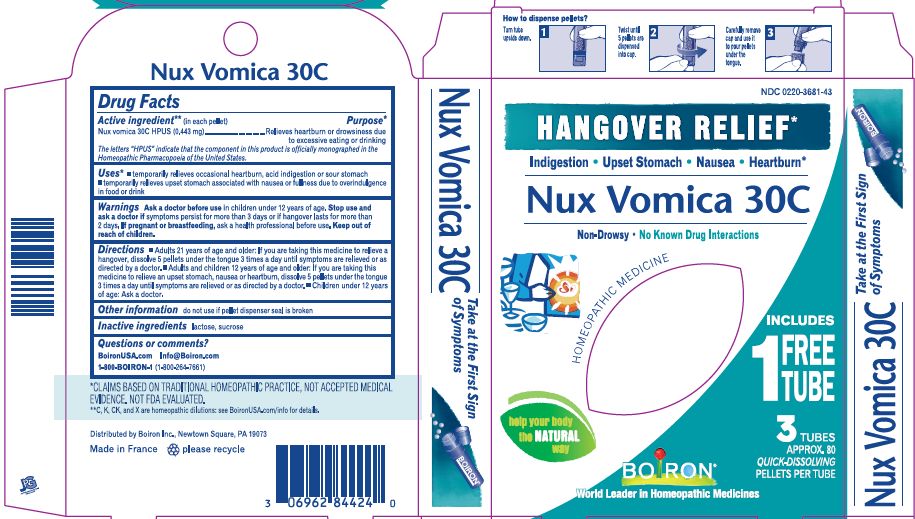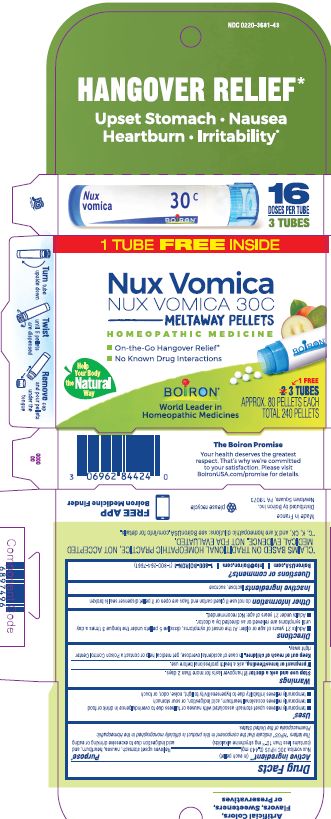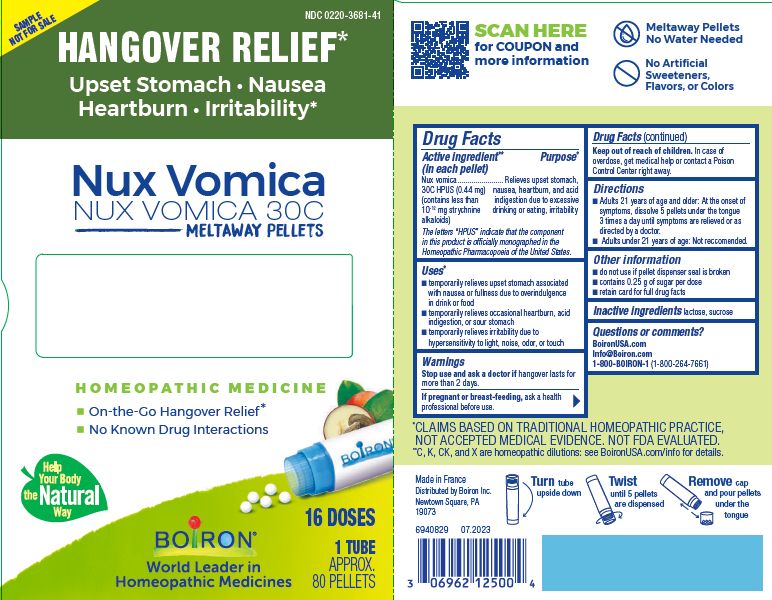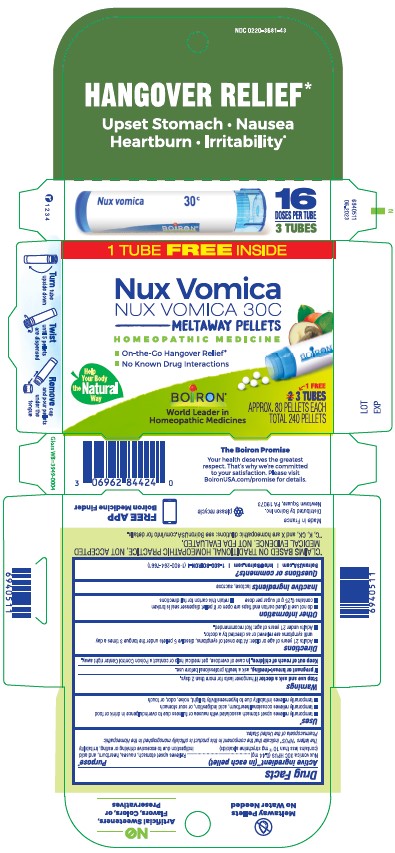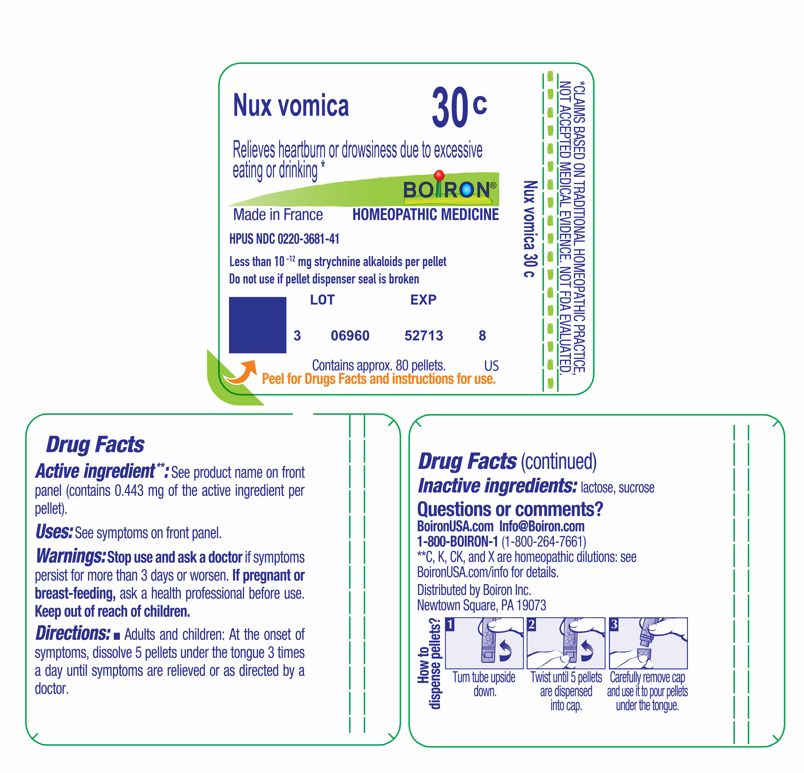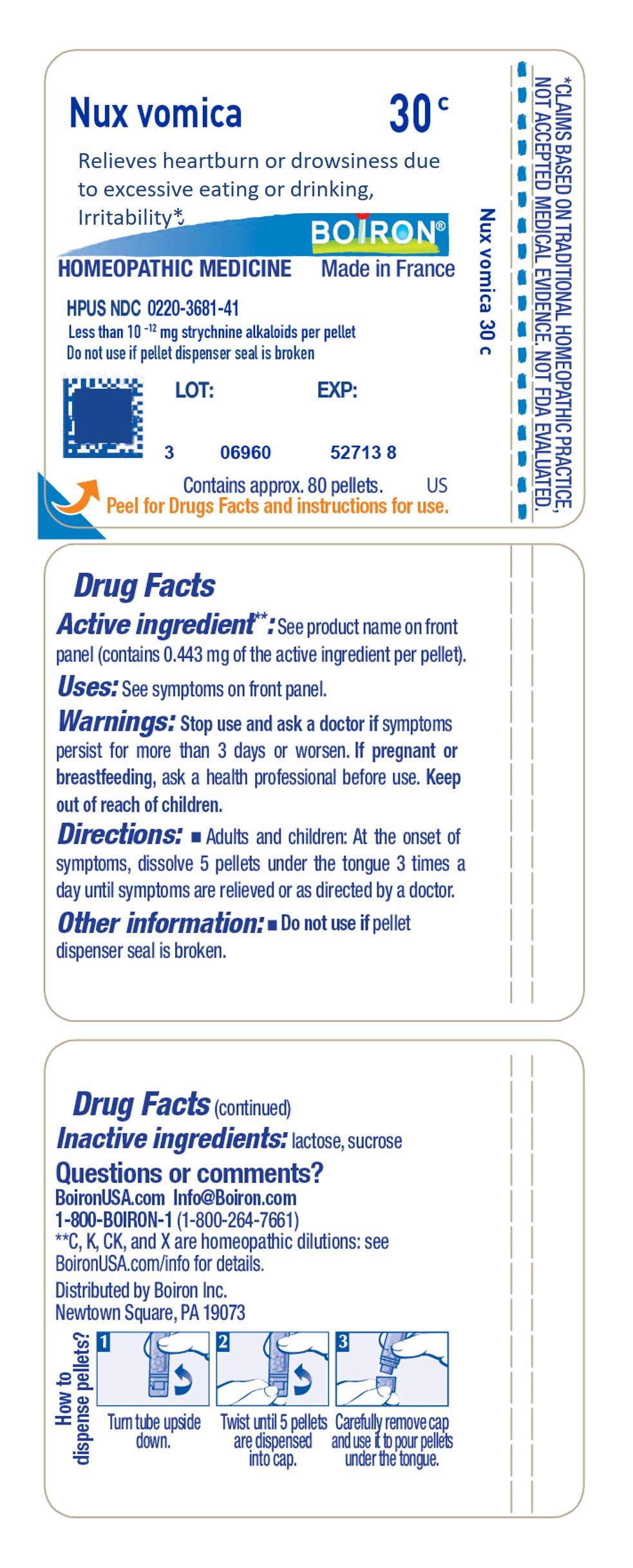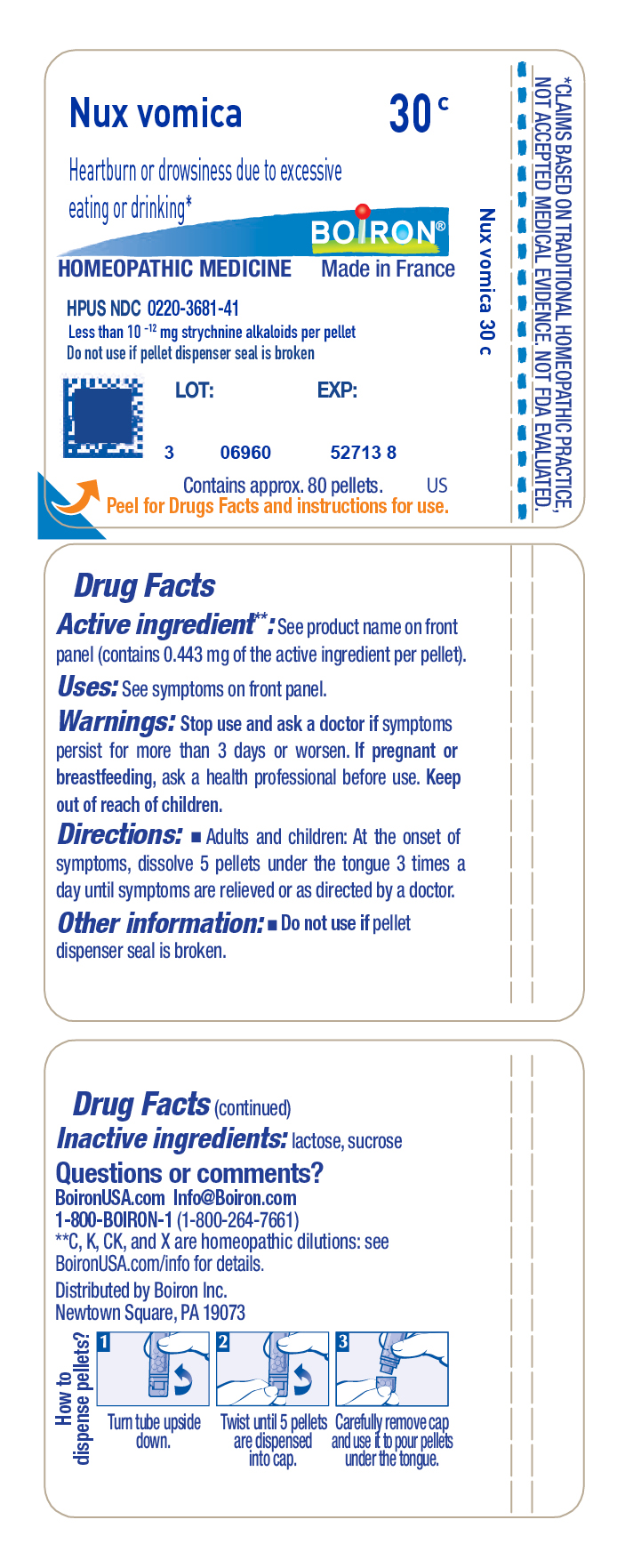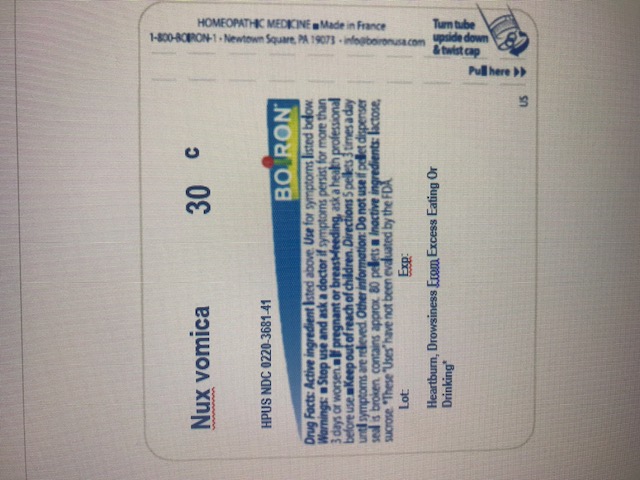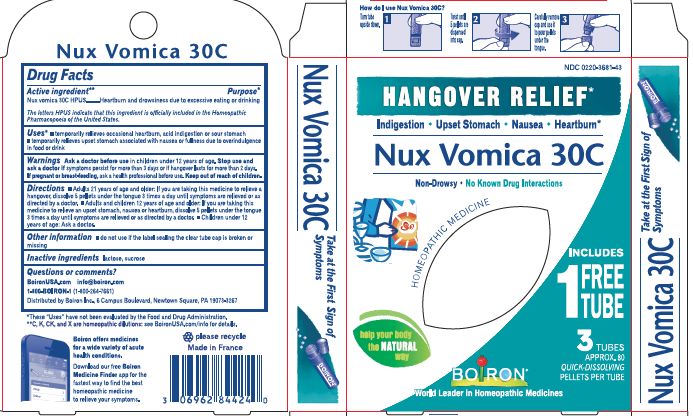 DRUG LABEL: Nux Vomica
NDC: 0220-3681 | Form: PELLET
Manufacturer: Laboratoires Boiron
Category: homeopathic | Type: HUMAN OTC DRUG LABEL
Date: 20240522

ACTIVE INGREDIENTS: STRYCHNOS NUX-VOMICA SEED 30 [hp_C]/1 1
INACTIVE INGREDIENTS: LACTOSE; SUCROSE

Nux vomica 30C B2G1

Active ingredient** (in each pellet)

Nux Vomica 30C HPUS
(**contains 0.44 mg of the active ingredient per pellet)

(contains less than 10^-12 strychnine alkaloids)

The letters "HPUS" indicate that the components in this product are officially monographed in the Homeopathic Pharmacopoeia of the United States.

PURPOSE

Relieves upset stomach, nausea, heartburn, and acid indigestion due to excessive drinking or eating, irritability

INDICATIONS AND USAGE

Hangover Relief Uses*

temporarily relieves upset stomach associated with nausea or fullness due to overindulgence in drink or food

temporarily relieves occasional heartburn, acid indigestion, or sour stomach

temporarily relieves irritability due to hypersensitivity to light, noise, odor or touch

Indigestion Relief Uses*

temporarily relieves upset stomach associated with nausea or fullness due to overindulgence in drink or food

temporarily relieves occasional heartburn, acid indigestion, or sour stomach

Tube Uses*

Relieves heartburn or drowsiness due to excessive eating or drinking, Irritability *

STOP USE

Hangover Relief

Stop use and ask a doctorif hangover lasts for more than 2 days.

Indigestion Relief

Stop use and ask a doctor if symptoms persist for more than 3 days or worsen. If you have trouble swallowing or persistent abdominal pain, see your doctor promptly.

PREGNANCY OR BREAST FEEDING

If pregnant or breast-feeding, ask a health professional before use.

Keep out of reach of children. In case of accidental overdose, get medical help or contact a Poison Control Center right away.

DOSAGE AND ADMINISTRATION

Hangover Relief

Adults 21 years of age or older: At the onset of symptoms, dissolve 5 pellets under the tongue 3 times a day until symptoms are relieved or as directed by a doctor.

Adults under 21 years of age: Not recommended.

Indigestion Relief

Adults and children 12 years age or older: At the onset of symptoms, dissolve 5 pellets under the tongue 3 times a day until symptoms are relieved or as directed by a doctor.

Children under 12 years of age: Ask a doctor.

Tube

Adults and children: At the onset of symptoms, dissolve 5 pellets under the tongue 3 times a day until symptoms are relieved or as directed by a doctor.

INACTIVE INGREDIENT

lactose, sucrose

Hangover Relief*

On-the-Go Hangover Relief*

No Known Drug Interactions

Upset Stomach Nausea Heartburn Irritability*

do not use if glued carton end flaps are open or if pellet dispenser seal is broken

contains 0.25 g of sugar per dose
retain this carton for full directions
Turn tube upside down. Twist until 5 pellets are dispensed. Remove cap and pour pellets under the tongue.

Approx. 80 pellets each

Total 240 pellets

3 Tubes

16 Doses

Indigestion Relief*

Upset or Sour Stomach Heartburn Nausea*

No Known Drug Interactions

do not use if glued carton end flaps are open or if pellet dispenser seal is broken

contains 0.25 g of sugar per dose
retain this carton for full directions
Turn tube upside down. Twist until 5 pellets are dispensed. Remove cap and pour pellets under the tongue.

Approx. 80 pellets each

Total 240 pellets

3 Tubes

*CLAIMS BASED ON TRADITIONAL HOMEOPATHIC PRACTICE NOT ACCEPTED MEDICAL EVIDENCE. NOT FDA EVALUATED.
*C,K,CK, and X are homeopathic dilutions: see BoironUSA.com/info for details.

Questions, Comments?
BoironUSA.com
info@boiron.com

1-800-BOIRON-1
(1-800-264-7661)

Distributed by Boiron Inc.
Newtown Square, PA 19073-3267